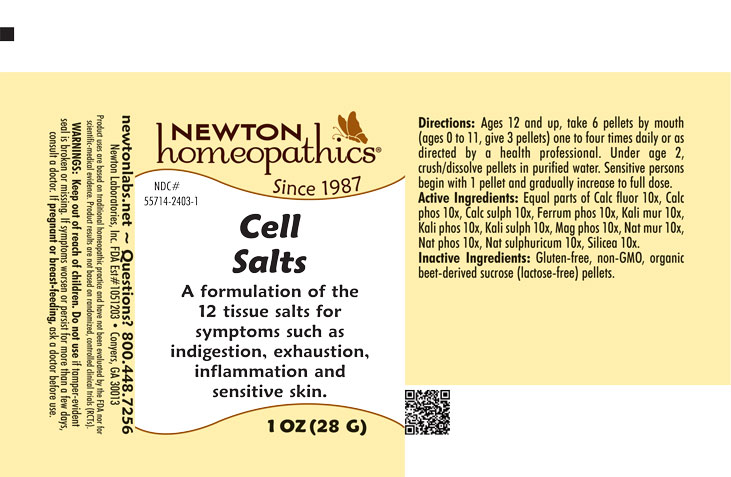 DRUG LABEL: Cell Salts
NDC: 55714-2403 | Form: PELLET
Manufacturer: Newton Laboratories, Inc.
Category: homeopathic | Type: HUMAN OTC DRUG LABEL
Date: 20250724

ACTIVE INGREDIENTS: CALCIUM FLUORIDE 10 [hp_X]/1 g; TRIBASIC CALCIUM PHOSPHATE 10 [hp_X]/1 g; CALCIUM SULFATE ANHYDROUS 10 [hp_X]/1 g; FERROSOFERRIC PHOSPHATE 10 [hp_X]/1 g; POTASSIUM CHLORIDE 10 [hp_X]/1 g; POTASSIUM PHOSPHATE, DIBASIC 10 [hp_X]/1 g; POTASSIUM SULFATE 10 [hp_X]/1 g; MAGNESIUM PHOSPHATE, DIBASIC TRIHYDRATE 10 [hp_X]/1 g; SODIUM CHLORIDE 10 [hp_X]/1 g; SODIUM PHOSPHATE, DIBASIC, HEPTAHYDRATE 10 [hp_X]/1 g; SODIUM SULFATE 10 [hp_X]/1 g; SILICON DIOXIDE 10 [hp_X]/1 g
INACTIVE INGREDIENTS: SUCROSE

Cell 2403P

OTC - PREGNANCY OR BREAST FEEDING SECTION

If pregnant or breast-feeding, ask a doctor before use.

OTC - KEEP OUT OF REACH OF CHILDREN SECTION

Keep out of reach of children.

WARNINGS SECTION

WARNINGS: Keep out of reach of children. Do not use if tamper-evident seal is broken or missing. If symptoms worsen or last for more than a few day, consult a doctor. If pregnant or breast-feeding, ask a doctor before use.

QUESTIONS SECTION

newtonlabs.net - Questions? 800 448-7256

Newton Laboratories, Inc. FDA Est # 1051203 - Conyers, GA 30013

INACTIVE INGREDIENT SECTION

Gluten-free, non-GMO, organic beet-derived sucrose (lactose-free) pellets.

OTC - PURPOSE SECTION

A formulation of the 12 tissue salts for symptoms such as indigestion, exhaustion, inflammation, and sensitive skin.

OTC - ACTIVE INGREDIENT SECTION

Equal parts of Calc. fluor. 10x, Calc. phos. 10x, Calc.sulph. 10x, Ferrum phos. 10x, Kali mur. 10x, Kali phos. 10x, Kali sulph. 10x, Mag. phos. 10x, Nat. mur. 10x, Nat. phos. 10x, Nat.sulphuricum 10x, Silicea 10x.

DOSAGE & ADMINISTRATION SECTION

Ages 12 and up, take 6 pellets by mouth (ages 0 to 11, take 3 pellets) one to four times daily or as directed by a health professional. Under age 2, crush/dissolve pellets in purified water. Sensitive persons begin with 1 pellet and gradually increase to full dose.

INDICATIONS & USAGE SECTION

A formulation of the 12 tissue salts for symptoms such as indigestion, exhaustion, inflammation and sensitive skin.